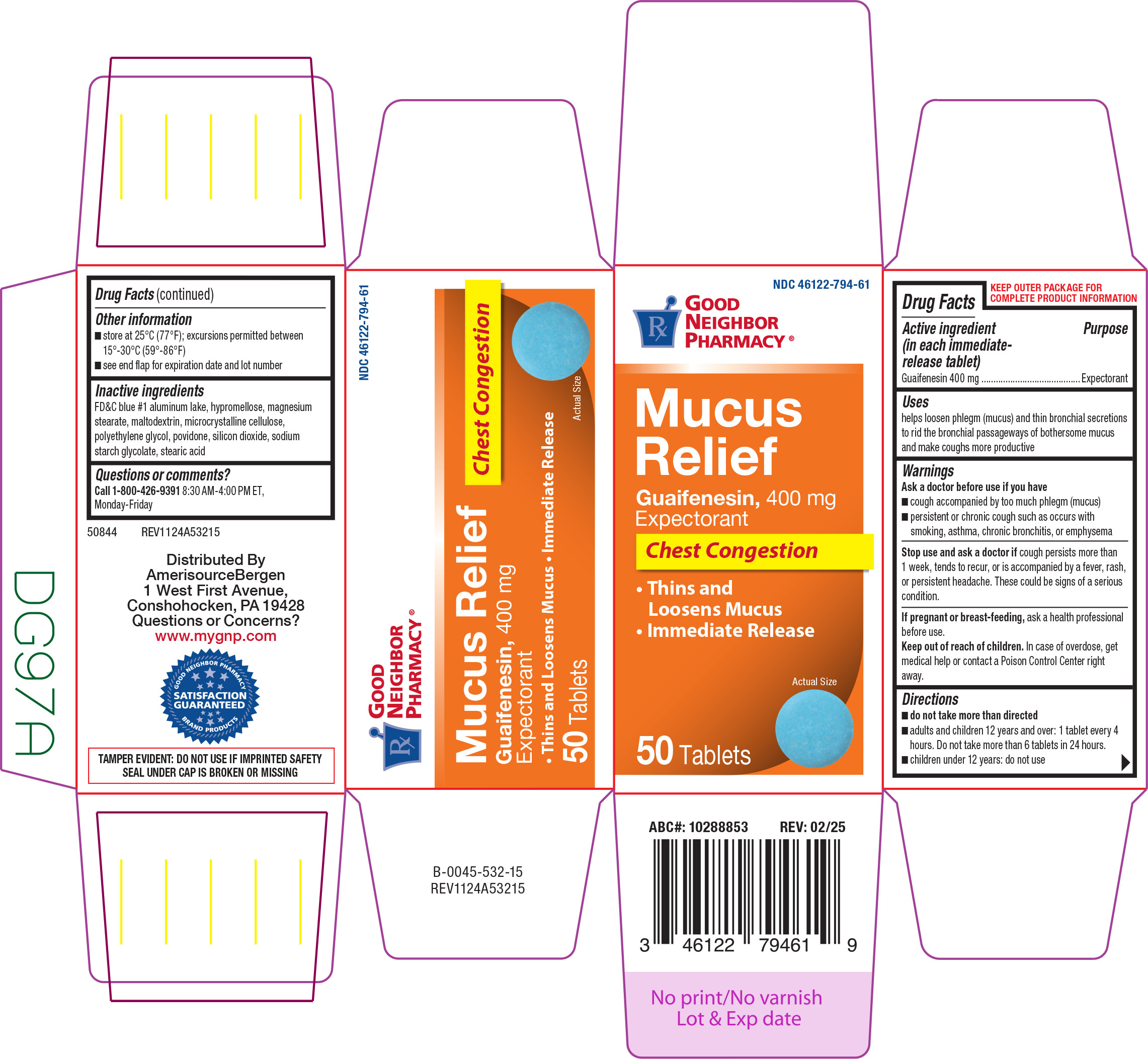 DRUG LABEL: Mucus Relief
NDC: 46122-794 | Form: TABLET, FILM COATED
Manufacturer: Amerisource Bergen
Category: otc | Type: HUMAN OTC DRUG LABEL
Date: 20250321

ACTIVE INGREDIENTS: GUAIFENESIN 400 mg/1 1
INACTIVE INGREDIENTS: FD&C BLUE NO. 1 ALUMINUM LAKE; HYPROMELLOSE, UNSPECIFIED; MAGNESIUM STEARATE; MALTODEXTRIN; MICROCRYSTALLINE CELLULOSE; POLYETHYLENE GLYCOL, UNSPECIFIED; POVIDONE, UNSPECIFIED; SILICON DIOXIDE; SODIUM STARCH GLYCOLATE TYPE A POTATO; STEARIC ACID

Good Neighbor Pharmacy 44-532

Active ingredient (in each immediate-release tablet)

Guaifenesin 400 mg

Purpose

Expectorant

Uses

helps loosen phlegm (mucus) and thin bronchial secretions to rid the bronchial passageways of bothersome mucus and make coughs more productive

Warnings

Ask a doctor before use if you have

- cough accompanied by too much phlegm (mucus)
- persistent or chronic cough such as occurs with smoking, asthma, chronic bronchitis, or emphysema

Stop use and ask a doctor if

cough persists more than 1 week, tends to recur, or is accompanied by a fever, rash, or persistent headache. These could be signs of a serious condition.

If pregnant or breast-feeding,

ask a health professional before use.

Keep out of reach of children.

In case of overdose, get medical help or contact a Poison Control Center right away.

Directions

- do not take more than directed
- adults and children 12 years and over: 1 tablet every 4 hours. Do not take more than 6 tablets in 24 hours.
- children under 12 years: do not use

Other information

- store at 25°C (77°F); excursions permitted between 15°-30°C (59°-86°F)
- see end flap for expiration date and lot number

Inactive ingredients

FD&C blue #1 aluminum lake, hypromellose, magnesium stearate, maltodextrin, microcrystalline cellulose, polyethylene glycol, povidone, silicon dioxide, sodium starch glycolate, stearic acid

Questions or comments?

Call 1-800-426-9391 8:30 AM-4:00 PM ET, Monday-Friday

Principal Display Panel

GOOD
NEIGHBOR
PHARMACY®

NDC 46122-794-61

Mucus Relief
Guaifenesin, 400 mg
Expectorant

Chest Congestion

• Thins and Loosens Mucus • Immediate Release

50 Tablets

Actual Size

TAMPER EVIDENT: DO NOT USE IF IMPRINTED SAFETY
SEAL UNDER CAP IS BROKEN OR MISSING

50844 REV1124A53215

Distributed By
AmerisourceBergen
1 West First Avenue,
Conshohocken, PA 19428
Questions or Concerns?
www.mygnp.com

SATISFACTION
GUARANTEE

God neighbor 44-532